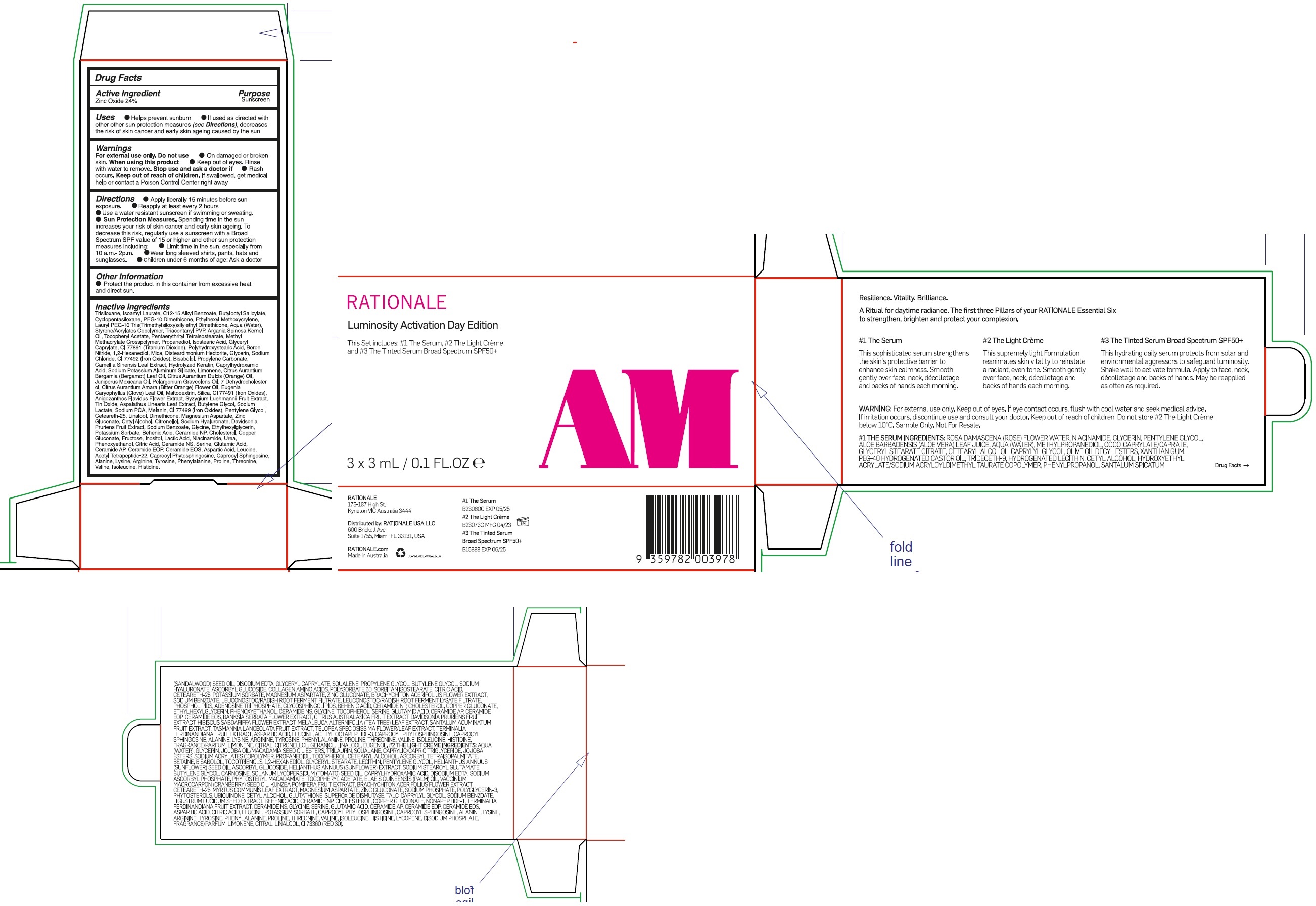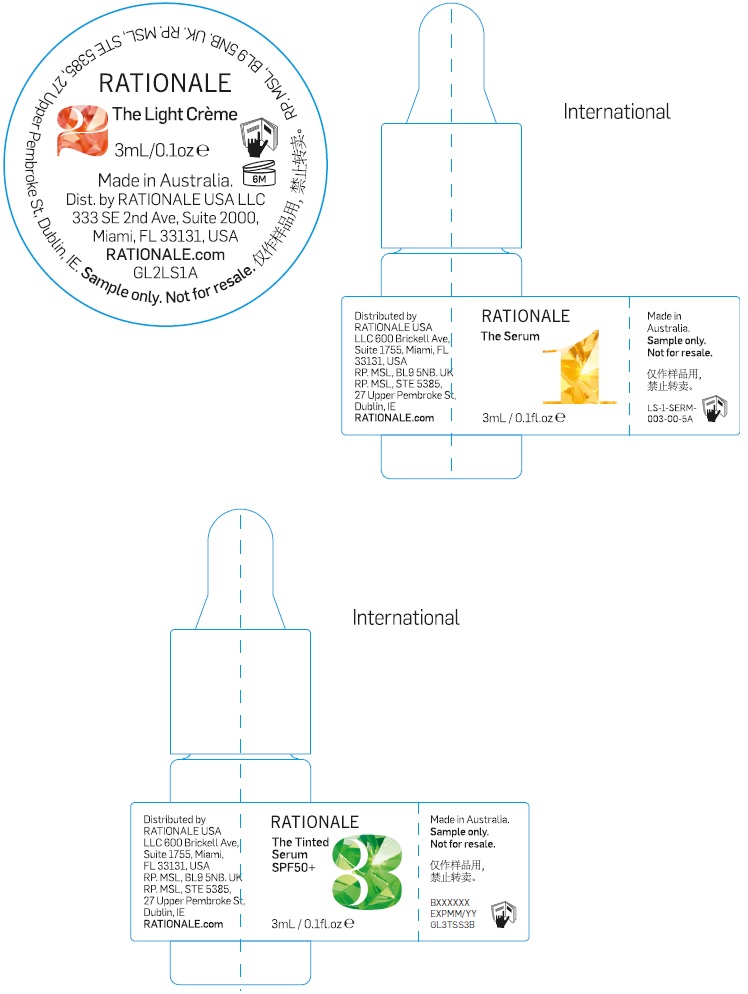 DRUG LABEL: Luminosity Activation Day Edition
NDC: 83108-100 | Form: KIT | Route: TOPICAL
Manufacturer: Rationale Group Pty Ltd
Category: otc | Type: HUMAN OTC DRUG LABEL
Date: 20251203

ACTIVE INGREDIENTS: ZINC OXIDE 240 mg/1 mL
INACTIVE INGREDIENTS: TRISILOXANE; ISOAMYL LAURATE; ALKYL (C12-15) BENZOATE; BUTYLOCTYL SALICYLATE; CYCLOMETHICONE 5; ETHYLHEXYL METHOXYCRYLENE; WATER; LYSINE; TRICONTANYL POVIDONE; ARGAN OIL; .ALPHA.-TOCOPHEROL ACETATE; PENTAERYTHRITYL TETRAISOSTEARATE; PROPANEDIOL; ISOSTEARIC ACID; GLYCERYL CAPRYLATE; TITANIUM DIOXIDE; BORON NITRIDE; 1,2-HEXANEDIOL; MICA; DISTEARDIMONIUM HECTORITE; GLYCERIN; SODIUM CHLORIDE; FERRIC OXIDE YELLOW; LEVOMENOL; PROPYLENE CARBONATE; GREEN TEA LEAF; CAPRYLHYDROXAMIC ACID; LIMONENE, (+)-; CITRUS BERGAMIA LEAF OIL; ORANGE OIL, COLD PRESSED; JUNIPERUS DEPPEANA WOOD OIL; GERANIUM OIL, ALGERIAN TYPE; 7-DEHYDROCHOLESTEROL; CITRUS AURANTIUM FLOWER OIL; CLOVE LEAF OIL; MALTODEXTRIN; SILICON DIOXIDE; FERRIC OXIDE RED; ANIGOZANTHOS FLAVIDUS FLOWERING TOP; SYZYGIUM LUEHMANNII FRUIT; STANNIC OXIDE; ASPALATHUS LINEARIS LEAF; BUTYLENE GLYCOL; SODIUM LACTATE; SODIUM PYRROLIDONE CARBOXYLATE; FERROSOFERRIC OXIDE; PENTYLENE GLYCOL; CETEARETH-25; LINALOOL, (+/-)-; DIMETHICONE; MAGNESIUM ASPARTATE; ZINC GLUCONATE; CETYL ALCOHOL; .BETA.-CITRONELLOL, (R)-; HYALURONATE SODIUM; DAVIDSONIA PRURIENS FRUIT; SODIUM BENZOATE; GLYCINE; ETHYLHEXYLGLYCERIN; POTASSIUM SORBATE; BEHENIC ACID; CERAMIDE NP; CHOLESTEROL; COPPER GLUCONATE; FRUCTOSE; INOSITOL; LACTIC ACID; NIACINAMIDE; UREA; PHENOXYETHANOL; CITRIC ACID MONOHYDRATE; CERAMIDE NG; SERINE; GLUTAMIC ACID; CERAMIDE AP; 3-DEHYDROXY CERAMIDE 1; ASPARTIC ACID; LEUCINE; CAPROOYL PHYTOSPHINGOSINE; N-HEXANOYLSPHINGOSINE; ALANINE; ARGININE; TYROSINE; PHENYLALANINE; DIPIVEFRIN HYDROCHLORIDE; THREONINE; VALINE; ISOLEUCINE; HISTIDINE

Luminosity Activation Day Edition

Active Ingredient

Zinc Oxide 24%

Purpose

Sunscreen

Uses

- Helps prevent sunburn.
- If used as directed with other sun protection measures (see Directions), decreases the risk of skin cancer and early skin ageing caused by the sun.

Warnings

For external use only.

Do not use

- On damaged or broken skin.

When using this product

- Keep out of eyes. Rinse with water to remove.

Stop use and ask a doctor if

- Rash occurs.

Keep out of reach of children.

- If swallowed, get medical help or contact a Poison Control Center right away.

Directions

- Apply liberally 15 minutes before sun exposure.
- Reapply
- At least every 2 hours
- Use a water resistant sunscreen if swimming or sweating.
- Sun Protection Measures.Spending time in the sun increases your risk of skin cancer and early skin ageing. To decrease this risk, regularly use a sunscreen with a Broad Spectrum SPF value of 15 or higher and other sun protection measures including:
- Limit time in the sun, especially from 10 a.m -2p.m.
- Wear long sleeved shirts, pants, hats and sunglasses.
- Children under 6 months of age: Ask a doctor.

Other Information

- Protect the product in this container from excessive heat and direct sun.

Inactive ingredients

Trisiloxane, Isoamyl Laurate, C12-15 Alkyl Benzoate, Butyloctyl Salicylate, Cyclopentasiloxane, PEG-10 Dimethicone, Ethylhexyl Methoxycrylene, Lauryl PEG-10 Tris (Trimethylsiloxy) silylethyl Dimethicone, Aqua (Water), Styrene/Acrylates Copolymer, Triacontanyl PVP, Argania Spinosa Kernel Oil, Tocopheryl Acetate, Pentaerhthrityl Tetraisostearate, Methyl Methacrylate Crosspolymer, Propanediol, Isostearic Acid, Glyceryl Caprylate, CI 77891 (Titanium Dioxide), Polyhydroxystearic Acid, Boron Nitride, 1,2-Hexanediol, Mica, Disteardimonium Hectorite, Glycerin, Sodium Chloride, CI 77492 (Iron Oxides), Bisabolol, Propylene Carbonate, Camellia Sinensis Leaf Extract, Hydrolyzed Keratin, Caprylhydroxamic Acid, Sodium Potassium Aluminum Silicate, Limonene, Citrus Aurantium Bergamia (Bergamot) Leaf Oil, Citrus Aurantium Dulcis (Orange) Oil, Juniperus Mexicana Oil, Pelargonium Graveolens Oil, 7-Dehydrocholesterol, Citrus Aurantium Amara (Bitter Orange) Flower Oil, Eugenia Caryophyllus (Clove) Leaf Oil, Maltodextrin, Silica, CI 77491 (Iron Oxides), Anigozanthos Flavidus Flower Extract, Syzygium Luehmannii Fruit Extract, Tin Oxide, Aspalathus Linearis Leaf Extract, Butylene Glycol, Sodium Lactate, Sodium PCA, Melanin, CI 77499 (Iron Oxides), Pentylene Glycol, Ceteareth-25, Linalool, Dimethicone, Magnesium Aspartate, Zinc Gluconate, Cetyl Alcohol, Citronellol, Sodium Hyaluronate, Davidsonia Pruriens Fruit Extract, Sodium Benzoate, Glycine, Ethylhexylglycerin, Potassium Sorbate, Behenic Acid, Ceramide NP, Cholesterol, Copper Gluconate, Fructose, Inositol, Lactic Acid, Niacinamide, Urea, Phenoxyethanol, Citric Acid, Ceramide NS, Serine, Glutamic Acid, Ceramide AP, Ceramide EOP, Ceramide EOS, Asparic Acid, Leucine, Acetyl Tetrapeptide-22, Caprooyl Phytosphingosine, Caprooyl Sphingosine, Alanine, Lysine, Arginine, Tyrosine, Phenylalanine, Propine, Threonine, Valine, Isoleucine, Histidine